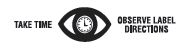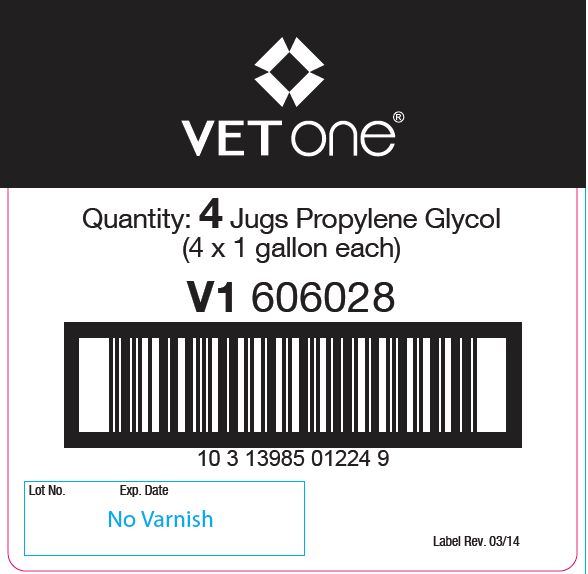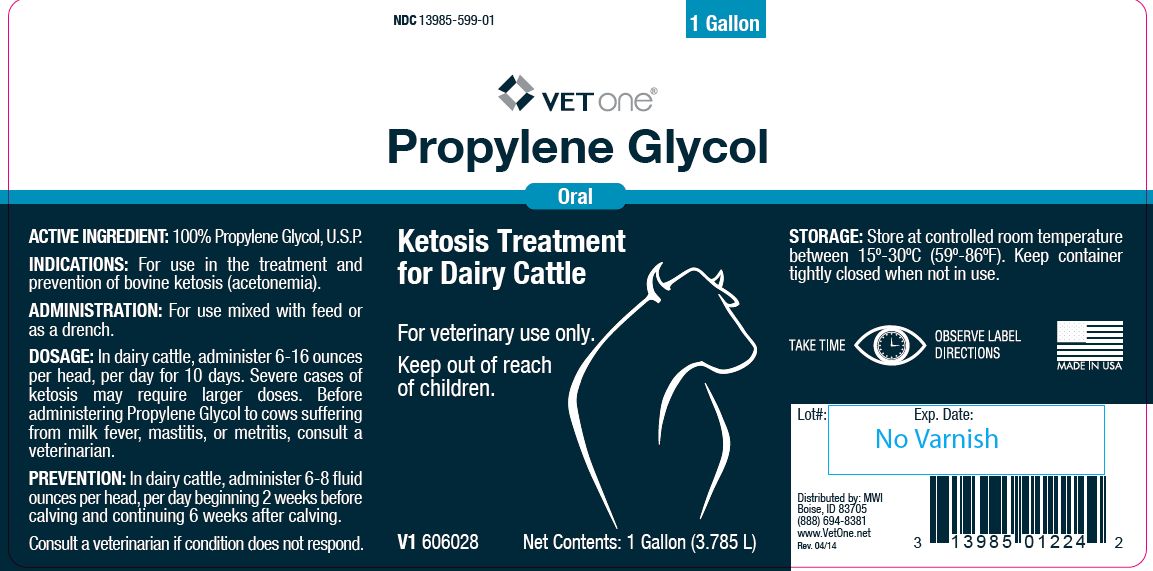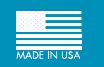 DRUG LABEL: PROPYLENE GLYCOL
NDC: 13985-599 | Form: LIQUID
Manufacturer: MWI/Vet One
Category: animal | Type: OTC ANIMAL DRUG LABEL
Date: 20241029

ACTIVE INGREDIENTS: PROPYLENE GLYCOL 1034.2 g/1 L

Propylene Glycol

PURPOSE

Oral

Ketosis Treatment for Dairy Cattle

KEEP OUT OF REACH OF CHILDREN

For veterinary use only.

Keep out of reach of children.

ACTIVE INGREDIENT:

100% Propylene Glycol, U.S.P.

INDICATIONS:

For use in the treatment and prevention of bovine ketosis (acetonemia).

DOSAGE:

In dairy cattle, administer 6-16 ounces per head, per day for 10 days. Severe cases of ketosis may require larger doses. Before administering Propylene Glycol to cows suffering from milk fever, mastitis, or metritis, consult a veterinarian.

PREVENTION:

In dairy cattle, administer 6-8 fluid ounces per head, per day beginning 2 weeks before calving and continuing 6 weeks after calving.

WARNINGS

Consult a veterinarian if condition does not respond.

STORAGE:

Store at controlled room temperature between 15º-30ºC (59º-86ºF). Keep container tightly closed when not in use.

Net Contents:

1 Gallon (3.785 L) V1 606028

INFORMATION FOR OWNERS/CAREGIVERS

Distributed by: MWI
Boise, ID 83705
(888) 694-8381
www.VetOne.net
Rev. 04/14